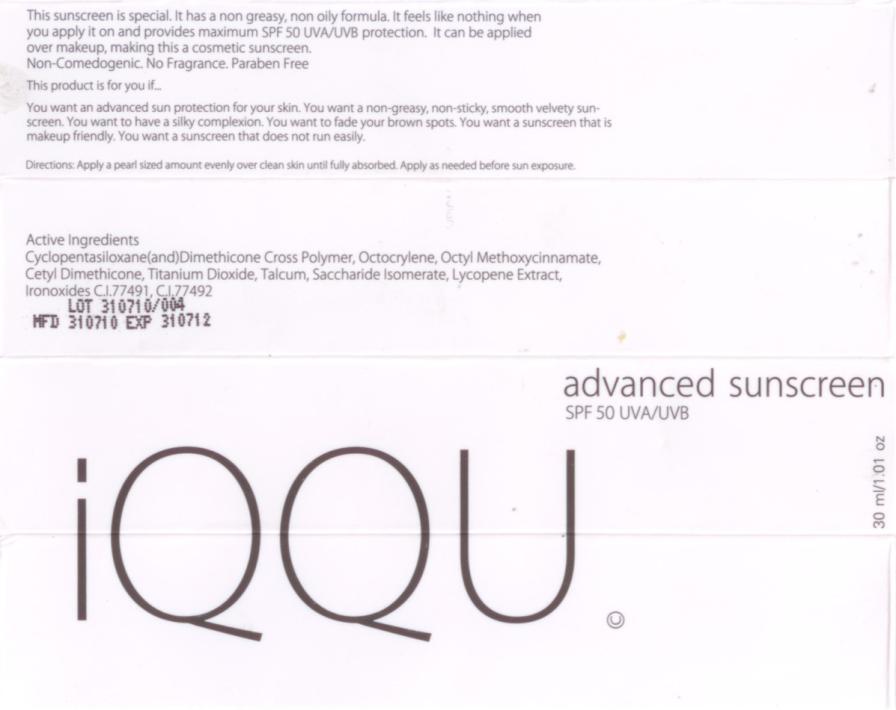 DRUG LABEL: IQQU Advanced Sunscreen SPF 50
NDC: 50403-050 | Form: LOTION
Manufacturer: IQQU USA Co.
Category: otc | Type: HUMAN OTC DRUG LABEL
Date: 20101203

ACTIVE INGREDIENTS: OCTINOXATE 0.9 g/0.03 g; JOJOBA OIL 1.5 g/0.05 g; TITANIUM DIOXIDE 0.9 g/0.03 g; .ALPHA.-TOCOPHEROL ACETATE, D- 0.3 g/0.01 g; LYCOPENE 0.3 g/0.01 g; SACCHARIDE ISOMERATE 0.3 g/0.01 g
INACTIVE INGREDIENTS: CYCLOMETHICONE 5; OCTOCRYLENE

Advanced Sunscreen SPF50

IQQU
Advance Sunscreen
SPF 50 UVA/UVB

Active Ingredient

Octyl Methoxycinnamate, Simmondsia Chinensis (jojoba) Seed oil, Titanium Dioxide, Tocopheryl Acetate, Saccharide Isomerate, Lycopene Extract

This sunscreen is special.

It has a non greasy, non oily formula. It feels like nothing when you apply it on and provides maximum SPF 50 UVA/UVB protection. It can be applied over makeup, making this a cosmetic sunscreen.

Non-Comedogenic. No Fragrance. Paraben Free

This product is for you if

You want an advanced sun protection for your skin. You want a non-greasy, non-sticky, smooth velvety sunscreen. You want to have a silky complexion. You want to fade your brown spots. you want a sunscreen that is makeup friendly. You want a sunscreen that does not run easily.

Directions

Advance formula, use a small amount only. Apply evenly over clean skin until fully absorbed. Apply as needed before sun exposure.

Keep the sunscreen tube away from direct sunlight to preserve its efficiency.

Warnings

For external use only. Avoid contact with the eyes. Discontinue use if signs of irritation occurs.

Inactive Ingredients

Cyclopentasiloxane (and) Dimethicone Cross Polymer, Octocrylene, Cetyl Dimethicone, Talcum, Ironoxides C.I. 77491, C.I. 77492

Manufactured by: June Laboratories Co., Ltd.
1014 Soi Wat Channai, Sathupradit Rd,
Bangkok 10120 Thailand.

Made in Thailand

www.iqqubeauty.com

PRINCIPAL DISPLAY PANEL

IQQU Advance Sunscreen

SPF 50 UVA/UVB

30 mL /1.01 oz